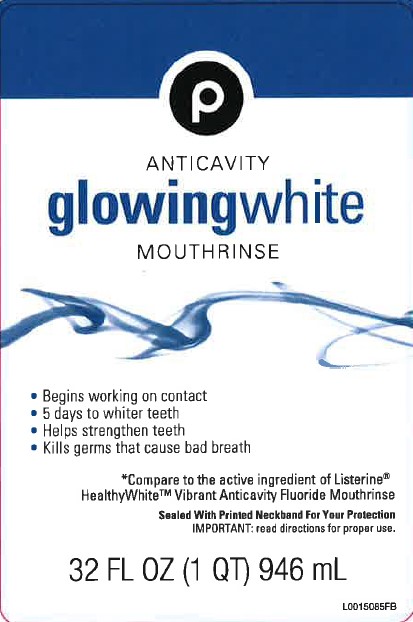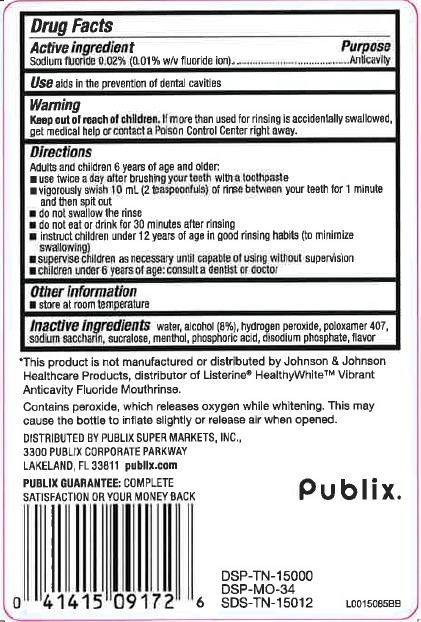 DRUG LABEL: Anticavity
NDC: 56062-435 | Form: MOUTHWASH
Manufacturer: Publix Super Markets, Inc.
Category: otc | Type: HUMAN OTC DRUG LABEL
Date: 20260205

ACTIVE INGREDIENTS: SODIUM FLUORIDE 0.1 mg/1 mL
INACTIVE INGREDIENTS: WATER; ALCOHOL; HYDROGEN PEROXIDE; POLOXAMER 407; SACCHARIN SODIUM; SUCRALOSE; MENTHOL; PHOSPHORIC ACID; SODIUM PHOSPHATE, DIBASIC, ANHYDROUS

Publix 435.000/435AA
Glowing White Anticavity Mouthrinse

Active Ingredient

Sodium fluoride 0.02% (0.01% w/v fluoride ion)

Purpose

Anticavity

Use

Aids in the prevention of dental cavities

Warnings

for this product

Keep out of reach of children.

If more than used for rinsing is accidentally swallowed, get medical help or contact a Poison Control Center right away.

Directions

Adults and children 6 years of age and older:

- use twice a day after brushing your teeth with a toothpaste
- vigorously swish 10 mL (2 teaspoonfuls) of rinse between your teeth for 1 minute and then spit out
- do not swallow the rinse
- do not eat or drink for 30 minutes after rinsing
- instruct children under 12 years of age in good rinsing habits (to minimize swallowing)
- supervise children as necessary until capable of using without supervision
- children under 6 years of age: consult a dentist or doctor

Other information

- store at room temperature.

Inactive ingredients

water, alcohol (8%), hydrogen peroxide, poloxamer 407, sodium saccharin, sucralose, menthol, phosphoric acid, disodium phosphate, flavor

Disclaimer

*This product is not manufactured or distributed by Johnson & Johnson Healthcare Products, distributor of Listerine® HealthyWhite™ Vibrant Anticavity Fluoride Mouthrinse.

Contains peroxide, which releases oxygen while whitening. This may cause the bottle to inflate slightly or release air when opened.

ADVERSE REACTION

Distributed by: Publix Super Markets, Inc.,

3300 Publix Corporate Parkway

Lakeland, FL 33811 publix.com

PUBLIX GUARANTEE: COMPLETE SATISFACTION OR YOUR MONEY BACK

Publix®

DSP-TN-15000

DSP-MO-34

SDS-TN-15012

Principal Display Panel

P

Antivavity

Glowing white

Mouthrinse

- Begins working on contact
- 5 days to whiter teeth
- Helps strengthen teeth
- Kills germs that cause bad breath

*Compare to the ingredients of Listerine®Healthywhite™ Vibrant Anticavity Fluoride Mouthrinse

Sealed with printed neckband for your protection

IMPORTANT: Read directions for proper use.

32 FL OZ (1 QT) 946 mL